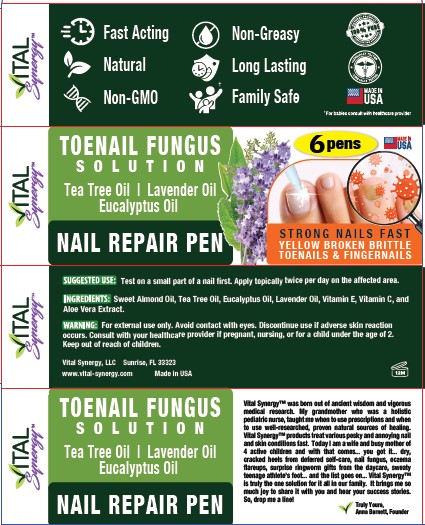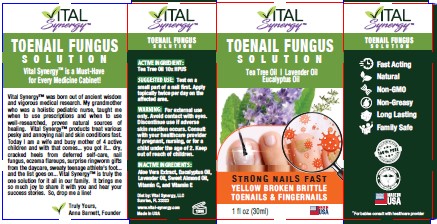 DRUG LABEL: TOENAIL FUNGUS / NAIL REPAIR PEN
NDC: 82743-101 | Form: SOLUTION
Manufacturer: VITAL SYNERGY LLC
Category: homeopathic | Type: HUMAN OTC DRUG LABEL
Date: 20220520

ACTIVE INGREDIENTS: TEA TREE OIL 10 [hp_X]/100 mL
INACTIVE INGREDIENTS: ALMOND OIL; TOCOPHEROL; ALOE VERA WHOLE; ASCORBIC ACID; EUCALYPTUS OIL; LAVENDER OIL

VITAL SYNERGY - TOENAIL FUNGUS SOLUTION / NAIL REPAIR PEN (82743-101)

ACTIVE INGREDIENT

TEA TREE OIL 10X HPUS

PURPOSE

ANTIFUNGAL

USES

STRONG NAILS FAST

YELLOW BROKEN BRITTLE TOENAILS & FINGERNAILS

WARNINGS

FOR EXTERNAL USE ONLY. AVOID CONTACT WITH EYES. DISCONTINUE USE IF ADVERSE SKIN REACTION OCCURS. CONSULT YOUR HEALTH CARE PHYSICIAN IF PREGNANT, NURSING, OR FOR A CHILD UNDER THE AGE OF TWO.

KEEP OUT OF REACH OF CHILDREN.

DIRECTIONS

TEST ON A SMALL PART OF A NAIL FIRST. APPLY TOPICALLY TWICE PER DAY ON THE AFFECTED AREA.

INACTIVE INGREDIENTS

ALOE VERA EXTRACT, EUCALYPTUS OIL, LAVENDER OIL, SWEET ALMOND OIL, VITAMIN C, AND VITAMIN E